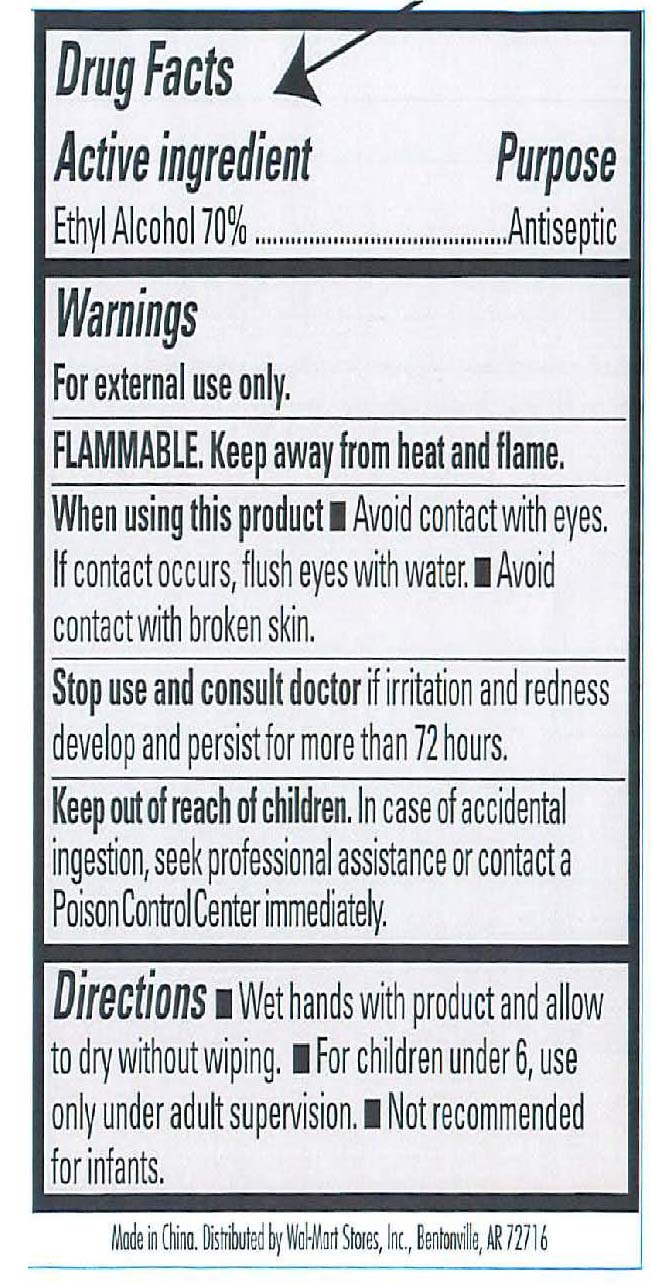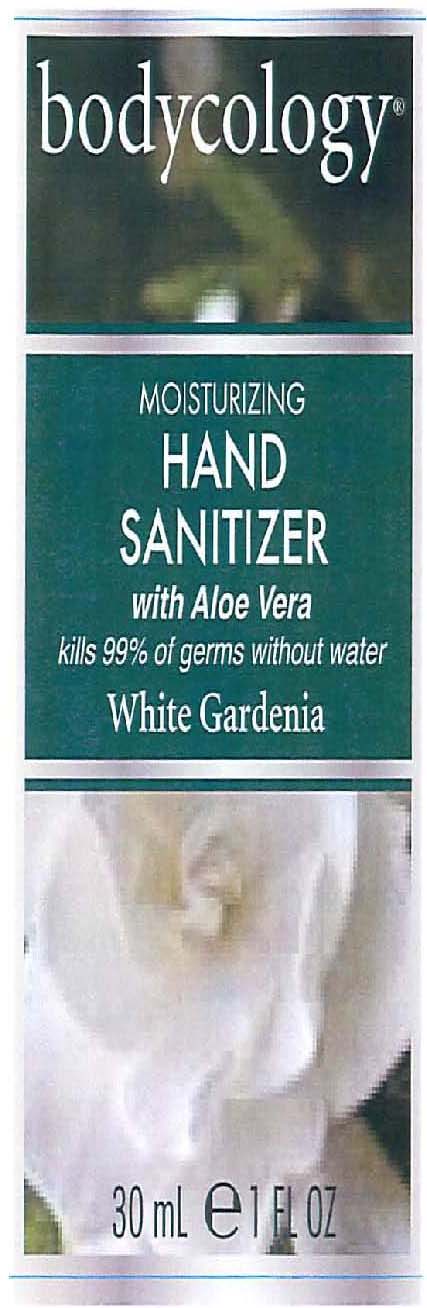 DRUG LABEL: Bodycology
NDC: 51706-205 | Form: GEL
Manufacturer: Landy International
Category: otc | Type: HUMAN OTC DRUG LABEL
Date: 20100709

ACTIVE INGREDIENTS: ALCOHOL 65 mL/100 mL

White Gardenia Hand Sanitizer

Active Ingredients

Ethyl Alcohol 65%

WARNINGS

Warnings: For external use only. When using this product do not get into eyes. If contact occurs, rinse eyes thoroughly with water. Keep out of reach of children. If swallowed, get medical help or contact a Poison Control Center right away.

INDICATIONS AND USAGE

Uses: to decrease bacteria on the skin that could cause disease.
Directions: wet hands, apply palmful to hands, scrub thoroughly for 30 seconds, rinse.

INACTIVE INGREDIENT

Inactive Ingredients: Water (Aqua), Isopropyl Myristate, Propylene Glycol, Triethanolamine, Carbomer, Fragrance (Parfum), Aloe Barbadensis (Aloe Vera) Leaf Juice, Yellow 5 (CI 19140), Ext. Violet 2 (CI 60730)

PACKAGE LABEL

White Gardenia Hand Sanitizer

30 ml 1 fl oz